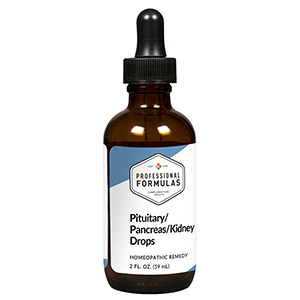 DRUG LABEL: Pituitary/Pancreas/Kidney Drops
NDC: 63083-5033 | Form: LIQUID
Manufacturer: Professional Complementary Health Formulas
Category: homeopathic | Type: HUMAN OTC DRUG LABEL
Date: 20190815

ACTIVE INGREDIENTS: ADIPIC ACID DIHYDRAZIDE 6 [hp_X]/59 mL; BEEF KIDNEY 6 [hp_X]/59 mL; BOS TAURUS PANCREAS 6 [hp_X]/59 mL; BOS TAURUS PITUITARY GLAND, POSTERIOR 6 [hp_X]/59 mL; KIDNEY BEAN 8 [hp_X]/59 mL; SYZYGIUM CUMINI SEED 9 [hp_X]/59 mL; LYCOPODIUM CLAVATUM SPORE 12 [hp_X]/59 mL; URANYL NITRATE HEXAHYDRATE 30 [hp_X]/59 mL
INACTIVE INGREDIENTS: ALCOHOL; WATER

HPPK

ACTIVE INGREDIENTS

Antidiuretic hormone (ADH) 6X
Kidney 6X, 12X, 30X, 60X, 100X
Pancreas 6X, 12X, 30X, 60X, 100X
Pituitary 6X, 12X, 30X, 60X, 100X
Phaseolus 8X
Syzygium jambolanum 9X
Lycopodium clavatum 12X
Uranium nitricum 30X

QUESTIONS

Professional Formulas

PO Box 2034 Lake Oswego, OR 97035

INDICATIONS

For the temporary relief of frequent urination, occasional headache, nausea or vomiting, or fatigue.*

PURPOSE

*Claims based on traditional homeopathic practice, not accepted medical evidence. Not FDA evaluated.

WARNINGS

Consult a doctor if condition worsens or if symptoms persist. Keep out of the reach of children. In case of overdose, get medical help or contact a poison control center right away. If pregnant or breastfeeding, ask a healthcare professional before use.

Keep out of the reach of children.

PREGNANCY OR BREAST FEEDING

If pregnant or breastfeeding, ask a healthcare professional before use.

DIRECTIONS

Place drops under tongue 30 minutes before/after meals. Adults and children 12 years and over: Take 10 drops up to 3 times per day. Consult a physician for use in children under 12 years of age.

OTHER INFORMATION

Tamper resistant. If seal is broken, do not use. After opening, close container tightly and store at room temperature away from heat.

INACTIVE INGREDIENTS

20% ethanol, purified water.

LABEL

Est 1985

Professional Formulas

Complementary Health

Pituitary/Pancreas/Kidney Drops

Homeopathic Remedy

2 FL. OZ. (59 mL)